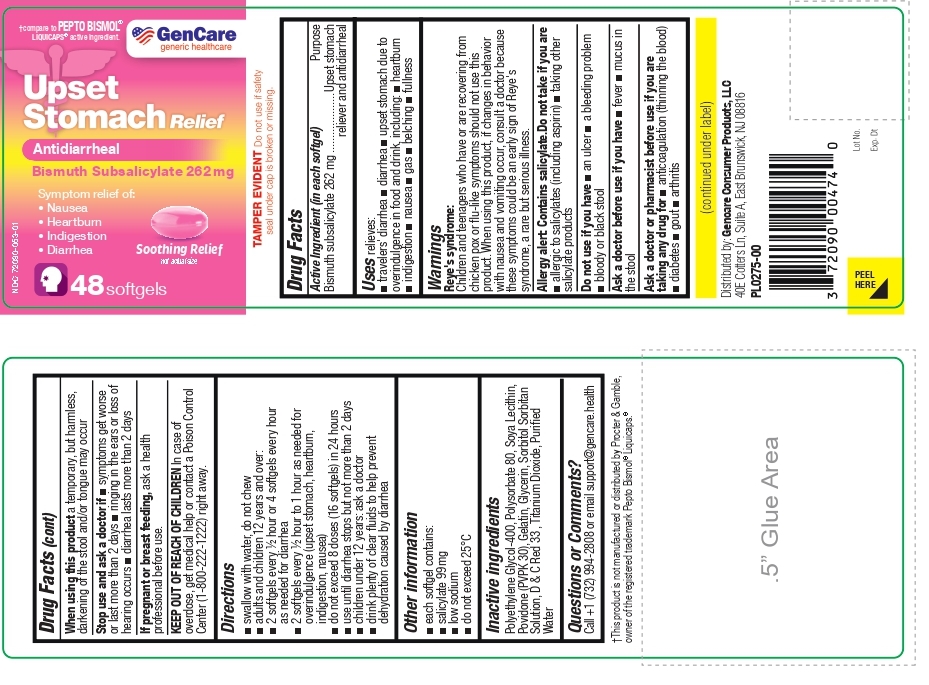 DRUG LABEL: Upset Stomach Relief-Bismuth Subsalicylate 262 mg
NDC: 72090-053 | Form: CAPSULE, LIQUID FILLED
Manufacturer: Pioneer Life Sciences, LLC
Category: otc | Type: HUMAN OTC DRUG LABEL
Date: 20250627

ACTIVE INGREDIENTS: BISMUTH SUBSALICYLATE 262 mg/1 1
INACTIVE INGREDIENTS: POLYETHYLENE GLYCOL 400; POLYSORBATE 80; SOYBEAN LECITHIN; POVIDONE K30; Gelatin; Glycerin; SORBITOL SOLUTION; SORBITAN; D&C RED NO. 33; Titanium Dioxide; WATER

Gencare-Upset Stomach Relief-Bismuth Subsalicylate 262 mg

Active Ingredient (in each softgel)

Bismuth subsalicylate 262 mg

Purpose

Upset stomach reliever and antidiarrheal

Uses

relieves:
■ travelers' diarrhea ■ diarrhea ■ upset stomach due to overindulgence in food and drink, including ■ heartburn ■ indigestion ■ nausea ■ gas ■ belching ■ fullness

Warnings

Reye's syndrome:
Children and teenagers who have or are recovering from chicken pox or flu-like symptoms should not use this product. When using this product, if changes in behavior with nausea and vomiting occur, consult a doctor because these symptoms could be an early sign of Reye's syndrome, a rare but serious illness.

Allergy alert: Contains salicylate.Do not take if you are ■ allergic to salicylates (including aspirin) ■ taking other salicylate products

Do not use if you have ■ an ulcer ■ a bleeding problem ■ bloody or black stool

Ask a doctor before use if you have ■ fever ■ mucus in the stool

Ask a doctor or pharmacist before use if you are taking any drug for ■ anticoagulation (thinning the blood) ■ diabetes ■ gout ■ arthritis

When using this product a temporary, but harmless, darkening of the stool and/or tongue may occur

Stop use and ask a doctor if ■ symptoms get worse or last more than 2 days ■ ringing in the ears or loss of hearing occurs ■ diarrhea lasts more than 2 days

PREGNANCY OR BREAST FEEDING

If pregnant or breast feeding, ask a health professional before use.

KEEP OUT OF REACH OF CHILDREN In case of overdose, get medical help or contact a Poison Control Center (1-800-222-1222) right away.

Directions

■ swallow with water, do not chew
■ adults and children 12 years and over:
■ 2 softgels every ½ hour or 4 softgels every hour as needed for diarrhea
■ 2 softgels every ½ hour to 1 hour as needed for overindulgence (upset stomach, heartburn, indigestion, nausea)
■ do not exceed 8 doses (16 softgels) in 24 hours
■ use until diarrhea stops but not more than 2 days
■ children under 12 years: ask a doctor
■ drink plenty of clear fluids to help prevent dehydration caused by diarrhea

Other information

■ each softgel contains:
■ salicylate 99 mg
■ low sodium
■ do not exceed 25°C

Inactive ingredients

Polyethylene Glycol-400, Polysorbate 80, Soya Lecithin, Povidone (PVPK 30), Gelatin, Glycerin, Sorbitol Sorbitan Solution, D & C Red 33 , Titanium Dioxide, Purified Water

Questions or Comments?

Call +1 (732) 994-2808 or email support@gencare.health